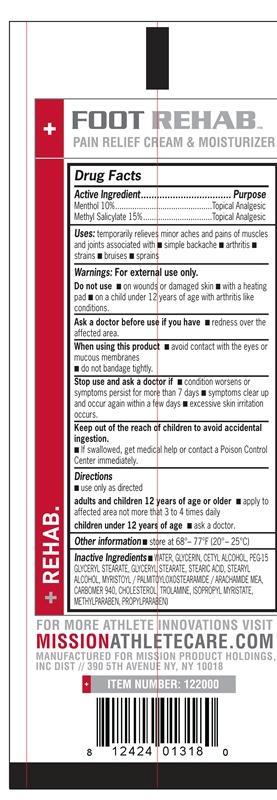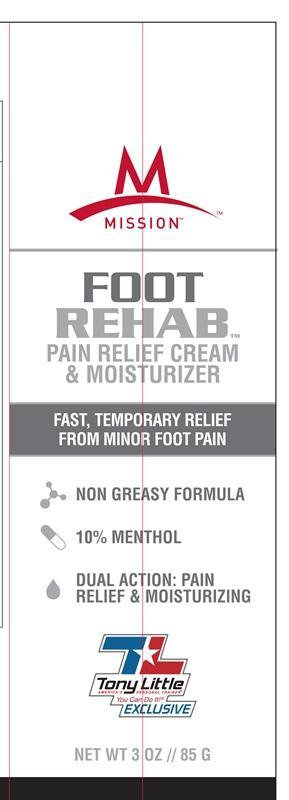 DRUG LABEL: Foot Rehab Pain relief and moisturizer
NDC: 76347-120 | Form: CREAM
Manufacturer: Mission Product Holdings
Category: otc | Type: HUMAN OTC DRUG LABEL
Date: 20130212

ACTIVE INGREDIENTS: MENTHOL 8.5 g/85 g; METHYL SALICYLATE 12.75 g/85 g
INACTIVE INGREDIENTS: WATER; GLYCERIN; CETYL ALCOHOL; PEG-15 GLYCERYL STEARATE; GLYCERYL MONOSTEARATE; STEARIC ACID; STEARYL ALCOHOL; MYRISTOYL/PALMITOYL OXOSTEARAMIDE/ARACHAMIDE MEA; CARBOMER HOMOPOLYMER TYPE C (ALLYL PENTAERYTHRITOL CROSSLINKED); CHOLESTEROL; TROLAMINE; ISOPROPYL MYRISTATE; METHYLPARABEN; PROPYLPARABEN

Foot Rehab

Active Ingredient Purpose

Menthol 10% Topical Analgesic

Methyl Salicylate 15 % Topical Analgesic

Uses:

Temporarily relieves minor aches and pains of muscles and joints associated with

- simple backache

- arthritis

- strains

- bruises

- sprains

KEEP OUT OF REACH OF CHILDREN

Keep out of the reach of children to avoid accidental ingestion.

If swallowed, get medical help or contact a Poison Control Center immediately.

Stop use and ask a doctor if

- condition worsens or symptoms persist for more than 7 days

- Symptoms clear up and occur again within a few days.

- excessive skin irritation occurs

Warnings

For external use only

Do not use on

- wounds or damaged skin

- with a heating pad

- on a child under 12 years of age with arthritis like conditions

Ask a doctor before use if you have redness over the affected area

Directions

-Use only as directed

adults and children 12 years of age or older

- Apply to affected area not more than 3 to 4 time daily.

Children under 12 years of age -ask a doctor

INACTIVE INGREDIENT

Inactive ingredients: Water, Glycerin, Cetyl aclohol, PEG-15 Glyceryl Stearate,Glyceryl Stearate, Stearic acid, Stearyl Alcohol, Myristoyl/palmitoyloxostearamide/Arachamide MEA, Carbomer 940, Cholesterol, Trolamine, Isopropyl Myristate, Methylparaben, Propylparaben.

PACKAGE LABEL

Mission

Foor Rehab™ Pain relief & moisturizer

fast temporary relief from minor foot pain

non greasy formula

10% Menthol

Dual Action: Pain relief & moisturizing

Net Wt 3 oz // 85 G